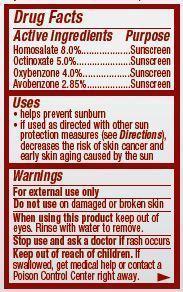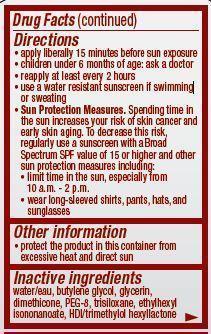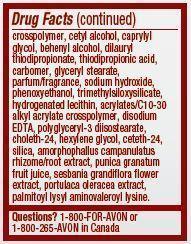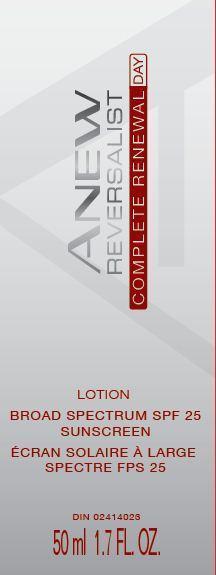 DRUG LABEL: Anew Reversalist
NDC: 10096-0311 | Form: LOTION
Manufacturer: New Avon LLC
Category: otc | Type: HUMAN OTC DRUG LABEL
Date: 20190101

ACTIVE INGREDIENTS: HOMOSALATE 80 mg/1 mL; OCTINOXATE 50 mg/1 mL; OXYBENZONE 40 mg/1 mL; AVOBENZONE 28.5 mg/1 mL
INACTIVE INGREDIENTS: WATER

Anew Reversalist Complete Renewal Day Lotion Broad Spectrum SPF 25

Active ingredient
Homosalate 8.0%..............
Octinoxate 5.0%...............
Oxybenzone 4.0%...........
Avobenzone 2.85%..........

Purpose
.................................Sunscreen

.................................Sunscreen

.................................Sunscreen

.................................Sunscreen

Uses
• helps prevent sunburn

• if used as directed with other sun protection measures (see Directions), decreases the risk of skin cancer and early skin aging caused by the sun

Warnings
For external use only

Do not use on damaged or broken skin

When using this product keep out of eyes. Rinse with water to remove.

Stop use and ask a doctor if rash occurs

Keep out of reach of children. If swallowed, get medical help or contact a Poison Control Center right away.

Directions
• apply liberally 15 minutes before sun exposure
• children under 6 months of age: ask a doctor
• reapply at least every 2 hours
• use a water resistant sunscreen if swimming or sweating
• Sun Protection Measures. Spending time in the sun increases your risk of skin cancer and early skin aging. To decrease this risk, regularly use a sunscreen with a Broad Spectrum SPF value of 15 or higher and other sun protection measures including:
• limit time in the sun, especially from 10 a.m. – 2 p.m.
• wear long-sleeved shirts, pants, hats, and sunglasses

Other information

• protect the product in this container from excessive heat and direct sun

Inactive Ingredients:
water/eau, butylene glycol, glycerin, dimethicone, PEG-8, trisiloxane, ethylhexyl isononanoate, HDI/trimethylol hexyllactone crosspolymer, cetyl alcohol, caprylyl glycol, behenyl alcohol, dilauryl thiodipropionate, thiodipropionic acid, carbomer, glyceryl stearate, parfum/fragrance, sodium hydroxide, phenoxyethanol, trimethylsiloxysilicate, hydrogenated lecithin, acrylates/C10-30 alkyl acrylate crosspolymer, disodium EDTA, polyglyceryl-3 diisostearate, choleth-24, hexylene glycol, ceteth-24, silica, amorphophallus campanulatus rhizome/root extract, punica granatum fruit juice, sesbania grandiflora flower extract, portulaca oleracea extract, palmitoyl lysyl aminovaleroyl lysine.

Questions?
1-800-FOR-AVON or 1-800-265-AVON in Canada